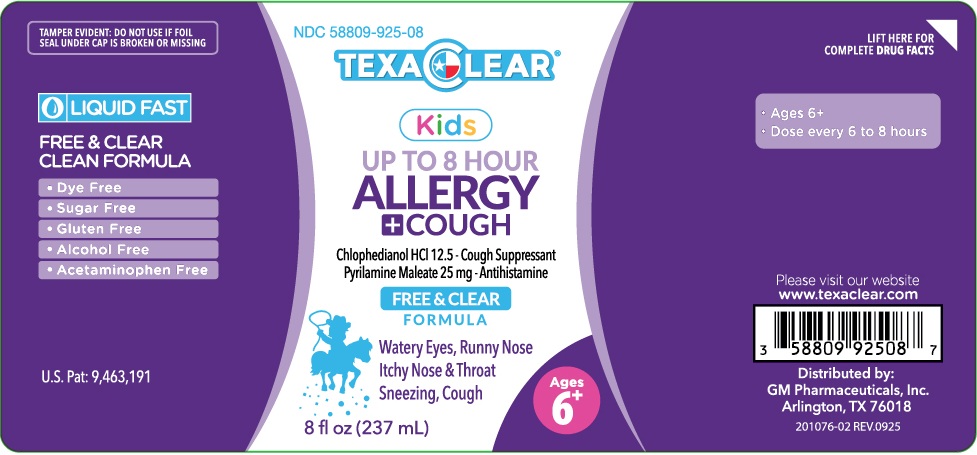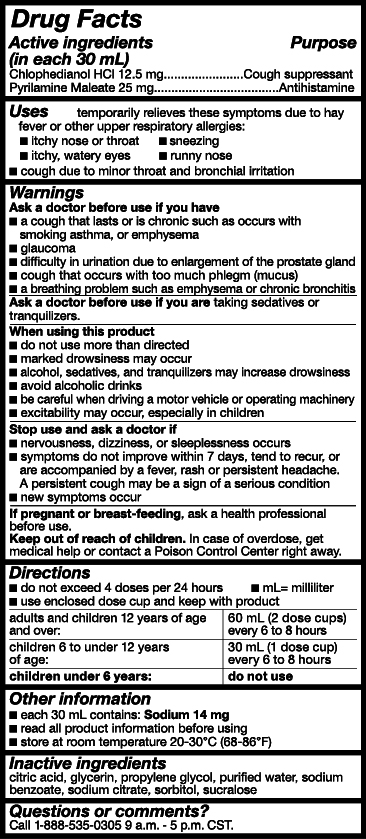 DRUG LABEL: TexaClear Kids Allergy
NDC: 58809-925 | Form: LIQUID
Manufacturer: GM Pharmaceuticals, Inc.
Category: otc | Type: HUMAN OTC DRUG LABEL
Date: 20251015

ACTIVE INGREDIENTS: CHLOPHEDIANOL HYDROCHLORIDE 12.5 mg/30 mL; PYRILAMINE MALEATE 25 mg/30 mL
INACTIVE INGREDIENTS: PROPYLENE GLYCOL; GLYCERIN; SODIUM BENZOATE; SODIUM CITRATE; ANHYDROUS CITRIC ACID; SORBITOL; SUCRALOSE; WATER

TexaClear Kids Allergy

Active Ingredients

(in each 30 mL (2 TBSP))

Chlophedianol HCl 12.5 mg

Pyrilamine Maleate 25 mg

Purpose

Cough Suppressant

Antihistamine

Uses

Temporarily relieves these symptoms due to the common cold, hay fever (allergic rhinitis) or other upper respiratory allergies:

- itchy nose or throat
- sneezing
- itchy, watery eyes
- runny nose
- cough due to minor throat and bronchial irritation

Warnings

Ask doctor before use if you have

- a cough that lasts or is chronic such as occurs with smoking, asthma, or emphysema
- glaucoma
- difficulty in urination due to the enlargment of the prostate gland
- cough that occurs with too much phlegm(mucus)
- a breathing problem such as emphysema or chronic bronchitis

Ask a doctor or pharmacist before use if you are

- taking sedative or tranquilizers

When using this product

- do not use more than directed
- marked drowsiniess may occur
- alcohol, secatives, and tranquilizers may increase drowsiness
- be careful when driving a motor vehicle or operating machinery
- excitability may occur, especiially in children

Stop use and ask a doctor if

- Nervousness, dizziness, or sleeplessness occurs
- symptoms do not improve within 7 days, tend to recur, or are accompanied by a fever, rash or persisten headace. A persisten cough may be a sign of a serious condition.
- new symptoms occur

PREGNANCY OR BREAST FEEDING

If pregnant or breast-feeding,as a health professional before use.

Keep out of reach of children.

In case of overdose, get medical help or contact a Poison Control Center right away.

Directions

- Do not exceed 4 doses per 24-hours.
- Use enclosed dose cup and keep with product.
- mL = mililiter

Adults and children 12 years of age and over: | 60 mL (2 dose cups) every 6 to 8 hours
Children 6 to under 12 years of age: | 30 mL (1 dose cup) every 6 to 8 hours
Children under 6 years of age: | Do not use.

Other Information

- each 30 mL contains: Sodium 14 mg
- read all product information before using
- store at room temperature 68-86°F (20-30°C

Inactive ingredients

citric acid, glycerin,propylene glycol, purified water, sodium benzoate, sodium citrate, sorbitol, sucralose

Questions or comments?

Call 1-888-535-0305 9 a.m. - 5 p.m. CST.

Distributed by:
GM Pharmaceuticals, Inc.
Arlington, TX 76018

KEEP LEAFLET AFTER OPENING

PACKAGE LABEL

TexaClear® Kids Allergy + Cough
NDC 58809-925-08
8 fl. oz. (237 mL)

Chlophedianol HCl – Cough Suppressant
Pyrilamine Maleate – Antihistamine

Tamper evident: do not use if foil seal under cap is broken on missing

- Gluten Free
- Dye Free
- Sugar Free
- Alcohol Free
- Acetaminophen Free

Ages 6+
Dose every 6 to 8 hours

- Sneezing
- Runny Nose
- Watery Eyes
- Itchy Nose & Throat
- Cough

Distributed by:
GM Pharmaceuticals, Inc.
Arlington, TX 76018